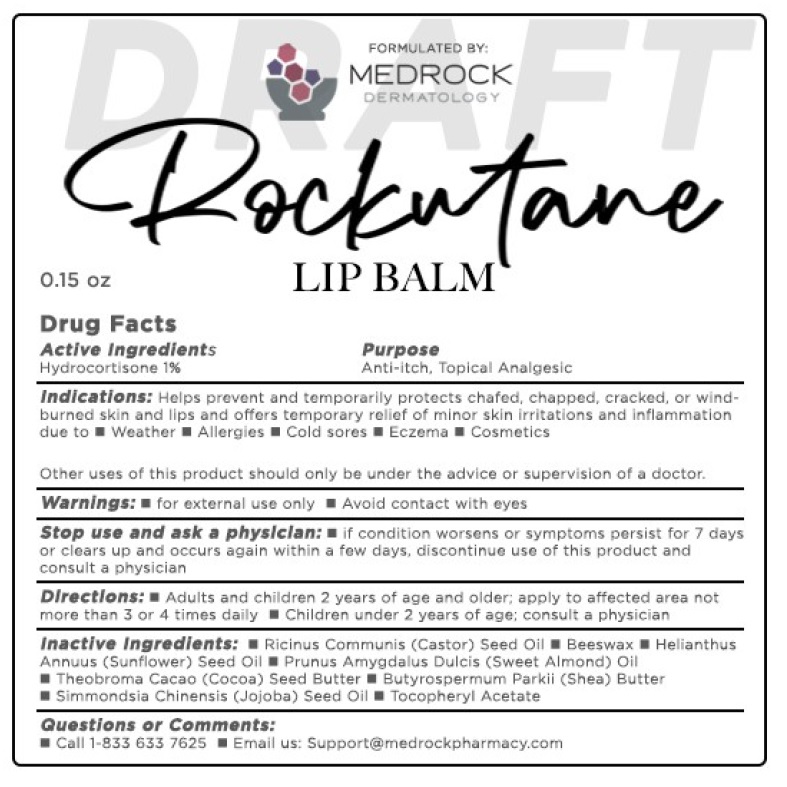 DRUG LABEL: Hydrocortisone
NDC: 85402-001 | Form: CREAM
Manufacturer: Medrock Pharmacy LLC
Category: otc | Type: HUMAN OTC DRUG LABEL
Date: 20260217

ACTIVE INGREDIENTS: HYDROCORTISONE 1 g/100 g
INACTIVE INGREDIENTS: RICINUS COMMUNIS (CASTOR) SEED OIL; BEESWAX; HELIANTHUS ANNUUS (SUNFLOWER) SEED OIL; PRUNUS AMYGDALUS DULCIS (SWEET ALMOND) OIL; THEOBROMA CACAO (COCOA) SEED BUTTER; BUTYROSPERMUM PARKII (SHEA) BUTTER; SIMMONDSIA CHINENSIS (JOJOBA) SEED OIL; .ALPHA.-TOCOPHEROL ACETATE

Drug Facts

Active ingredients

Hydrocortisone 1%

Purpose

Anti-itch, Topical Analgesic

Indications:

Helps prevent and temporarily protects chafed, chapped, cracked, or wind-burned skin and lips and offers temporary relief of minor skinirritations and inflammation due to

- Weather
- Allergies
- Cold sores
- Eczema
- Cosmetics

Other uses of this product should only be under the advice or supervision of a doctor.

Warnings:

- for external use only
- Avoid contact with eyes

Stop use and ask a physician:

- if condition worsens or symptoms persist for 7 days or clears up and occurs again within a few days, discontinue use of this product and consult a physician

Keep out of reach of children.

Directions:

- Adults and children 2 years of age and older; apply to affected area not more than 3 to 4 times daily
- Children under 2 years of age: consult a physician

For external anal itching:

- Adults: when practical, cleanse the affected area with mild soap and warm water and rinse thoroughly
- gently dry by patting or blotting with toilet tissue or a soft cloth before application of this product

Children under 12 years of age: consult a doctor

Inactive ingredients:

• Ricinus Communis (Castor) Seed Oil • Beeswax • Helianthus Annuus (Sunflower) Seed Oil • Prunus Amygdalus Dulcis (Sweet Almond) Oil
• Theobroma Cacao (Cocoa) Seed Butter • Butyrospermum Parkii (Shea) Butter • Simmondsia Chinensis (Jojoba) Seed Oil
• Tocopheryl Acetate

Questions or Comments:

- Call 1-833-633-7625
- Email us: support@medrockpharmacy.com